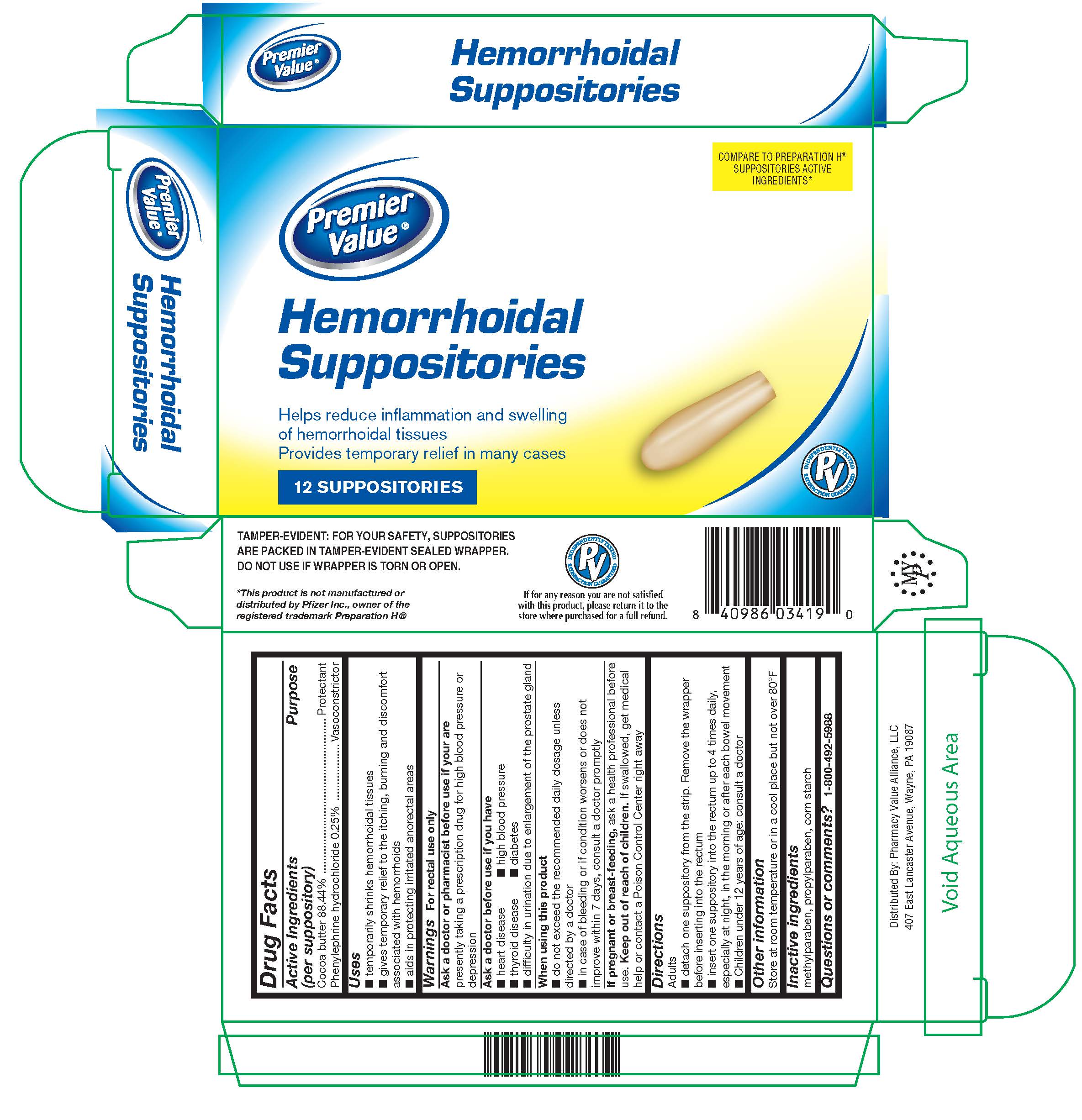 DRUG LABEL: Hemorrhoidal
NDC: 68016-322 | Form: SUPPOSITORY
Manufacturer: Pharmacy Value Alliance LLC
Category: otc | Type: HUMAN OTC DRUG LABEL
Date: 20251024

ACTIVE INGREDIENTS: COCOA BUTTER 2.39 g/1 1; PHENYLEPHRINE HYDROCHLORIDE 6.75 mg/1 1
INACTIVE INGREDIENTS: STARCH, CORN; METHYLPARABEN; PROPYLPARABEN

Premier Value Hemmorrhoidal Suppositories

Active Ingredients (per suppository)

Cocoa butter 88.44%

Phenylephrine hydrochloride 0.25%

Purpose

Protectant

Vasoconstrictor

Uses

- temporarily shrinks hemorrhoidal tissue
- gives temporary relief to the itching, burning and discomfort associated with hemorrhoids
- aids in protecting irritated anorectal areas

Warnings

For rectal use only

Ask a doctor or pharmacist before use if you are

presently taking a prescription drug for high blood pressure or depression

Ask a doctor before use if you have

- heart disease
- thyroid disease
- difficulty in urination due to enlargement of the prostate gland
- high blood pressure
- diabetes

When using this product

- do not exceed the recommended daily dosage unless directed by a doctor
- in case of bleeding or if condition worsens or does not improve within 7 days, consult a doctor promptly

If pregnant or breast-feeding,

ask a health professional before use.

Keep out of reach of children.

If swallowed, get medical help or contact a Poison Control Center right away

Directions

Adults

- detach one suppository from the strip. Remove the wrapper before inserting into the rectum
- insert one suppository into the rectum up to 4 times daily, especially at night, in the morning or after each bowel movement
- children under 12 years of age: consult a doctor

Other information

Store at room temperature or in a cool place but not over 80°F

Inactive ingredients

corn starch, methylparaben, propylparaben

Questions or comments?

1-800-492-5988

PACKAGE LABEL

The product package shown below represents a sample of that currently in use. Additional packaging may also be available.

Premier Value Hemorrhoidal Suppositories 12ct

Distributed by Pharmacy Value Alliance LLC

407 East Lancaster Avenue

Wayne, PA 19087

785PVHemSupp.jpg